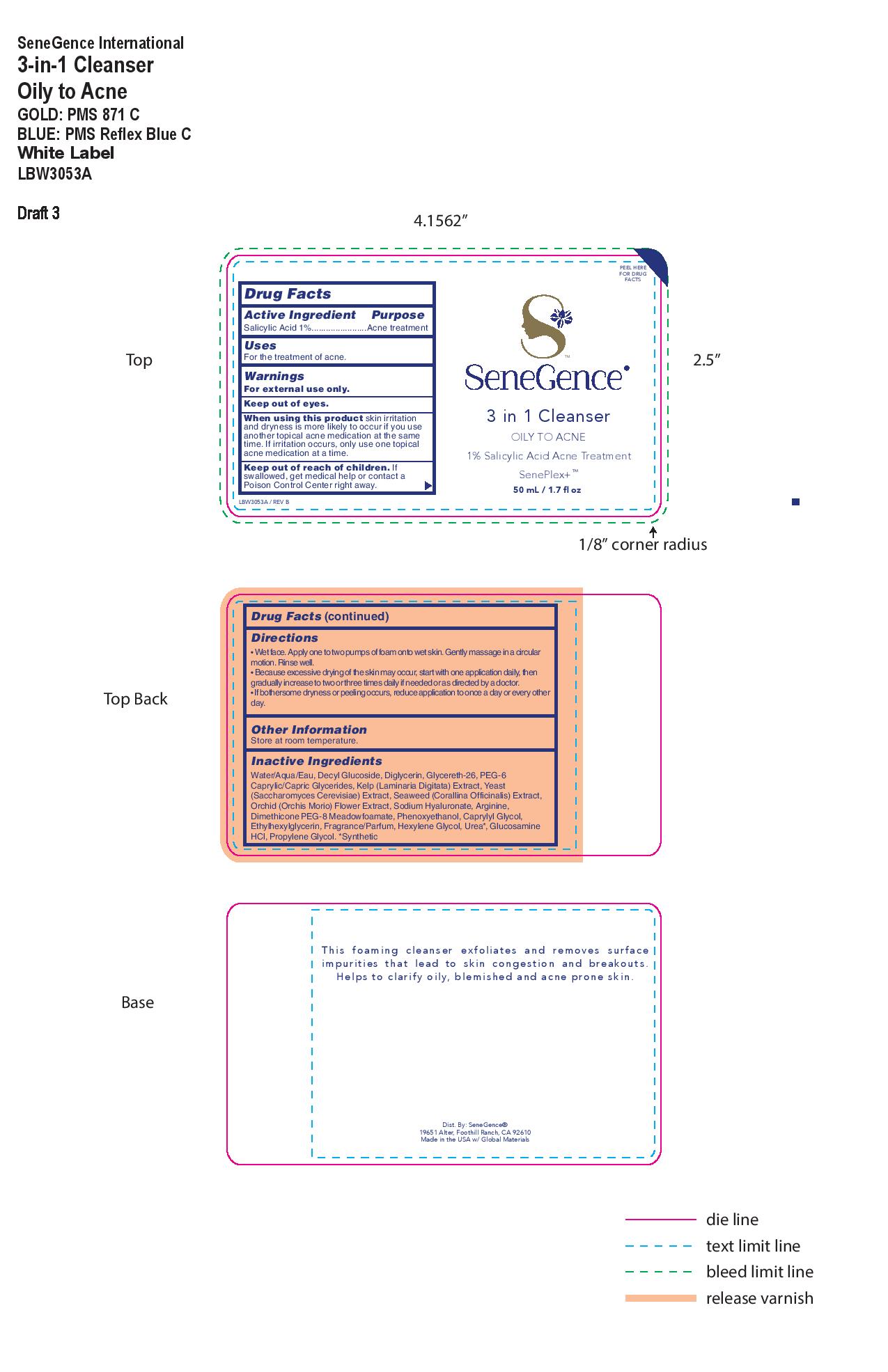 DRUG LABEL: 3 in 1 Cleanser
NDC: 72644-634 | Form: LIQUID
Manufacturer: SGII, INC.
Category: otc | Type: HUMAN OTC DRUG LABEL
Date: 20200916

ACTIVE INGREDIENTS: SALICYLIC ACID 1 g/100 g
INACTIVE INGREDIENTS: CAPRYLYL GLYCOL; ETHYLHEXYLGLYCERIN; ARGININE; FRAGRANCE CLEAN ORC0600327; HEXYLENE GLYCOL; PROPYLENE GLYCOL; DECYL GLUCOSIDE; HYALURONATE SODIUM; GLUCOSAMINE HYDROCHLORIDE; UREA; GLYCERETH-26; PEG-8 DIMETHICONE; PEG-6 CAPRYLIC/CAPRIC GLYCERIDES; LAMINARIA DIGITATA; ANACAMPTIS MORIO FLOWER; CORALLINA OFFICINALIS; WATER; PHENOXYETHANOL

Daily 3 in 1 Cleanser

Active Ingredients

Salicylic Acid 1%

Purpose

Salicylic Acid 1% ......Acne Treatment

Uses

For the treatment of acne.

Warnings

For External Use Only

Keep out of Eyes

When using this product skin irritation and dryness is more likely to occur if you use another topical acne medication at the same
time. If irritation occurs, only use one topical acne medication at a time.

Keep out of reach of children. If swallowed, get medical help or contact a Poison Control Center right away.

Directions

• Wet face. Apply one to two pumps of foam onto wet skin. Gently massage in a circular motion. Rinse well.
• Because excessive drying of the skin may occur, start with one application daily, then gradually increase to two or three times daily if needed or as directed by a doctor.
• If bothersome dryness or peeling occurs, reduce application to once a day or every other day.

Other Information

Store at room temperature.

Inactive Ingredients

Water/Aqua/Eau, Decyl Glucoside, Diglycerin, Glycereth-26, PEG-6 Caprylic/Capric Glycerides, Kelp (Laminaria Digitata) Extract, Yeast (Saccharomyces Cerevisiae) Extract, Seaweed (Corallina Officinalis) Extract, Orchid (Orchis Morio) Flower Extract, Sodium Hyaluronate, Arginine, Dimethicone PEG-8 Meadowfoamate, Phenoxyethanol, Caprylyl Glycol, Ethylhexylglycerin, Fragrance/Parfum, Hexylene Glycol, Urea*, Glucosamine HCl, Propylene Glycol. *Synthetic